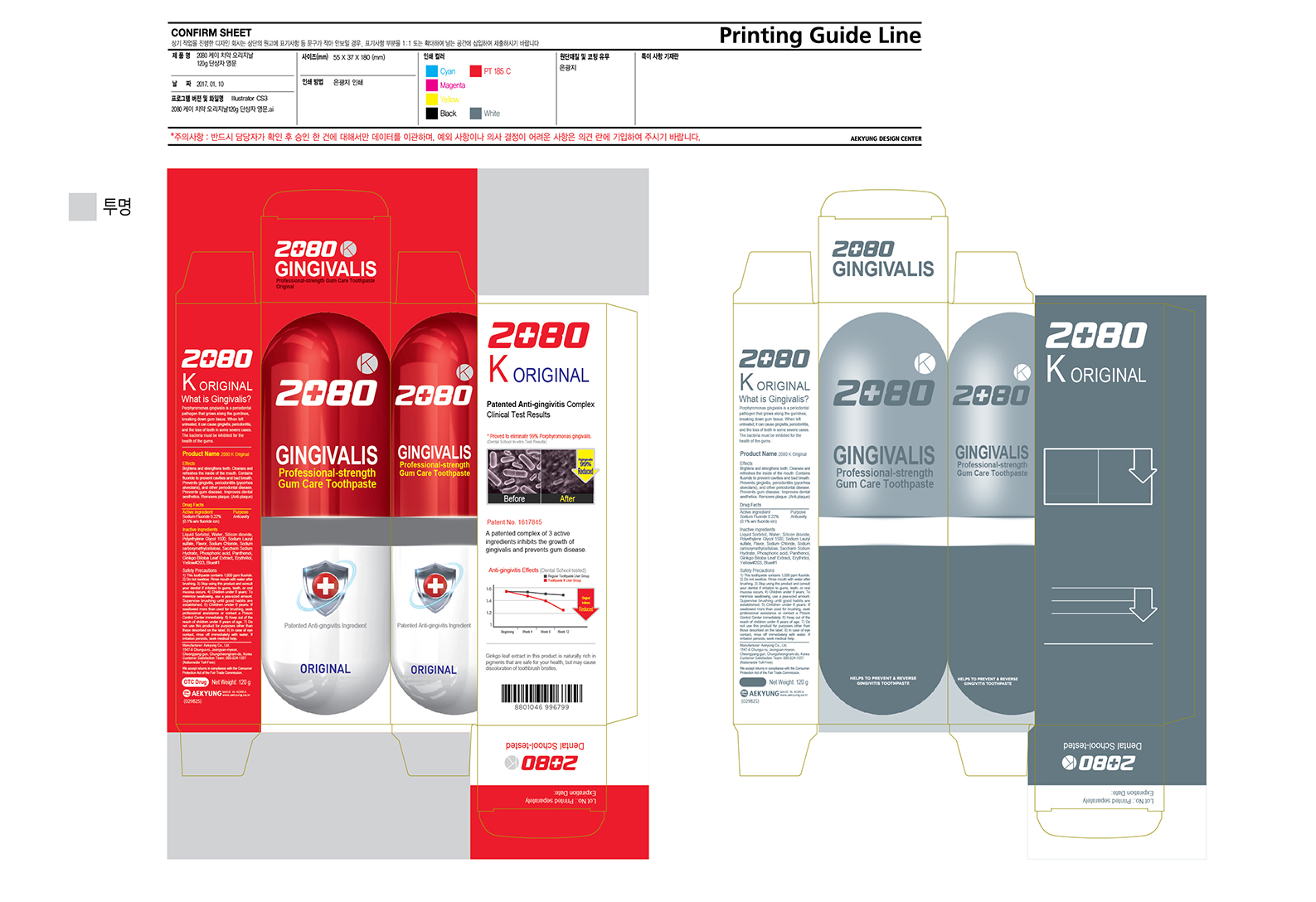 DRUG LABEL: 2080 K Original
NDC: 71401-0007 | Form: PASTE
Manufacturer: AK AMERICA
Category: otc | Type: HUMAN OTC DRUG LABEL
Date: 20170426

ACTIVE INGREDIENTS: SODIUM FLUORIDE 0.12 g/120 g
INACTIVE INGREDIENTS: SORBITOL 72 g/120 g; SODIUM LAURYL SULFATE 3.12 g/120 g; CARBOXYMETHYLCELLULOSE SODIUM 0.6 g/120 g; SACCHARIN SODIUM 0.156 g/120 g; SILICON DIOXIDE 0.12 g/120 g; PHOSPHORIC ACID 22.8 g/120 g; WATER 12.07 g/120 g; PANTHENOL 0.6 g/120 g; POLYETHYLENE GLYCOL 1500 0.006 g/120 g; FD&C BLUE NO. 1 0.00156 g/120 g; SODIUM CHLORIDE; GINKGO; ERYTHRITOL; D&C YELLOW NO. 10

Active Ingredient: Sodium Fluoride 0.22% (0.1% w/v fluoride)

Purpose: anticavity

Do not use this product for purposes other than those described on the label. In case of eye contact, rinse off immediately with water. If irritation persists, seek medical help.

KEEP OUT OF REACH OF CHILDREN

Keep out of the reach of children under 6 years of age

STOP USE

Stop using this product and consult your dentist if irritation to gums, teeth, or oral mucosa occurs

INDICATIONS AND USAGE

Do not swallow. Rinse mouth with water after brushing.

Children under 6 years:

- To minimize swallowing, use a pea-sized amount. Supervise brushing until good habits are established.

- If swallowed more than used for brushing, seek professional assistance or contact a Poison Control Center immediately.

DOSAGE AND ADMINISTRATION

This toothpaste contains 1,000 ppm fluoride

INACTIVE INGREDIENT

Inactive Ingredients: Liquid Sorbitor, Water, Silicon Dioxide, Polyethylene Glycol 1500, Sodium Lauryl Sulfate Flavor, Sodium Chloride, Sodium Carboxymethylcellulose, Saccharin Sodium Hydrate, Phosphoric Acid, Panthenol, Ginkgo Biloba Leaf Extract, Erythritol, Yellow#203, Blue#1